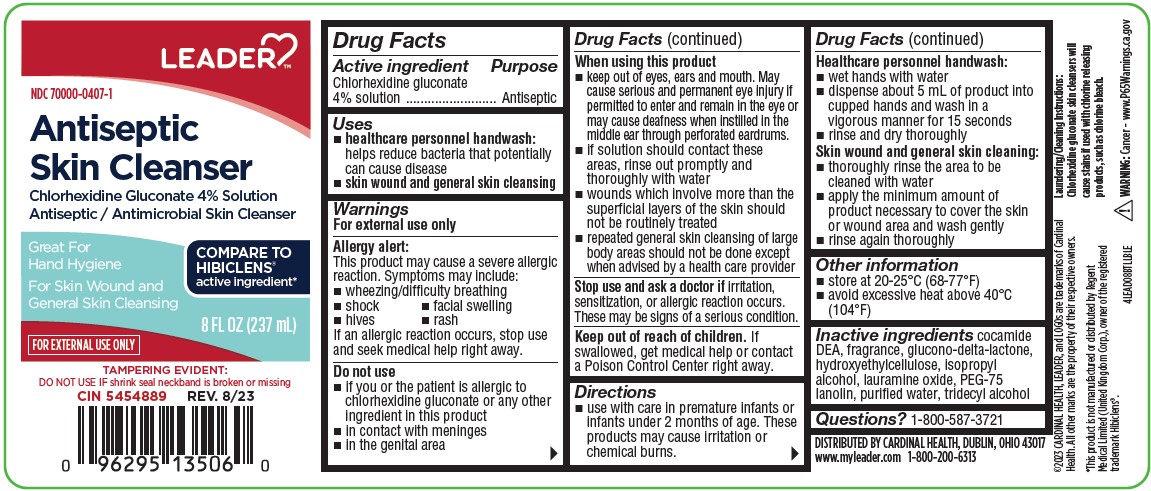 DRUG LABEL: Antiseptic Skin Cleanser
NDC: 70000-0407 | Form: LIQUID
Manufacturer: Cardinal Health
Category: otc | Type: HUMAN OTC DRUG LABEL
Date: 20251212

ACTIVE INGREDIENTS: CHLORHEXIDINE GLUCONATE 4 g/100 mL
INACTIVE INGREDIENTS: LAURAMINE OXIDE; PEG-75 LANOLIN; TRIDECYL ALCOHOL; GLUCONOLACTONE; HYDROXYETHYL CELLULOSE (2000 CPS AT 1%); ISOPROPYL ALCOHOL; COCO DIETHANOLAMIDE; WATER

COMP Cardinal Health Leader 4% CHG 8oz

Active ingredient

Chlorhexidine gluconate 4% solution

Purpose

Antiseptic

Uses

- healthcare personnel handwash: helps reduce bacteria that potentially can cause disease
- skin wound and general skin cleansing

Warnings

For external use only

Allergy alert:

This product may cause a severe allergic reaction. Symptoms may include:

- wheezing/difficulty breathing
- shock
- facial swelling
- hives
- rash

If an allergic reaction occurs, stop use and seek medical help right away.

Do not use

- if you or the patient is allergic to chlorhexidine gluconate or any other ingredient in this product
- in contact with meninges
- in the genital area

When using this product

- keep out of eyes, ears and mouth. May cause serious and permenant eye injury if permitted to enter and remain in the eye or may cause deafness when instilled in the middle ear through perforated eardrums.
- if solution should contact these areas, rinse out promptly and thoroughly with water
- wounds which involve more than the superficial layers of the skin should not be routinely treated
- repeated general skin cleansing of large body areas should not be done except advised by a health care provider

Stop use and ask a doctor if

irritation, sensitization, or allergic reaction occurs. These may be signs of a serious condition.

Keep out of reach of children

If swallowed, get medical help or contact a Poison Control Center right away.

Directions

- use with care in premature infants or infants under 2 months of age. These products may cause irritation of chemical burns.

Healthcare personnel handwash:

- wet hands with water
- dispense about 5 mL of product into cupped hands and wash in a vigorous manner for about 15 seconds
- rinse and dry thoroughly

Skin wound and general skin cleansing:

- thoroughly rinse the area to be cleaned with water
- apply the minimum amount of product necessary to cover the skin or wound area and wash gently
- rinse again thoroughly

Other information

- store at 20-25 ºC (68-77ºF)
- avoid excessive heat about 40ºC (104ºF)

Inactive ingredients

cocamide DEA, fragrance, glucono-delta-lactone, hydroxyethylcellulose, isopropyl alcohol, lauramine oxide, PEG-75 lanolin, purified water, tridecyl alcohol

Questions?

1-800-587-3721

OTHER SAFETY INFORMATION

Laundering/cleaning instructions:

Chlorhexidine gluconate skin cleansers will cause stains if used with chlorine releasing products, such as chlorine bleach.

*This product is not manufactured or districuted by Regent Medical Limited (United Kingdom Corp.), owner of the registered trademark Hibiclens ®.

WARNING: Cancer - www.P65Warnings.ca.gov

PDP

NDC 70000-0407-1

Leader

Antisptic Skin Cleanser

Chlorhexidine Gluconate 4% Solution

Antiseptic/Antimicrobial Skin Cleanser

Great For Hand Hygiene

For Skin Wound and General Skin Cleansing

Compare To Hibiclens® active ingredients*

For External Use Only

8 fl (237 mL)

Tampering evident:

Do not use if shrink seal neackband is broken or missing

CIN 5454889 REV. 8/23